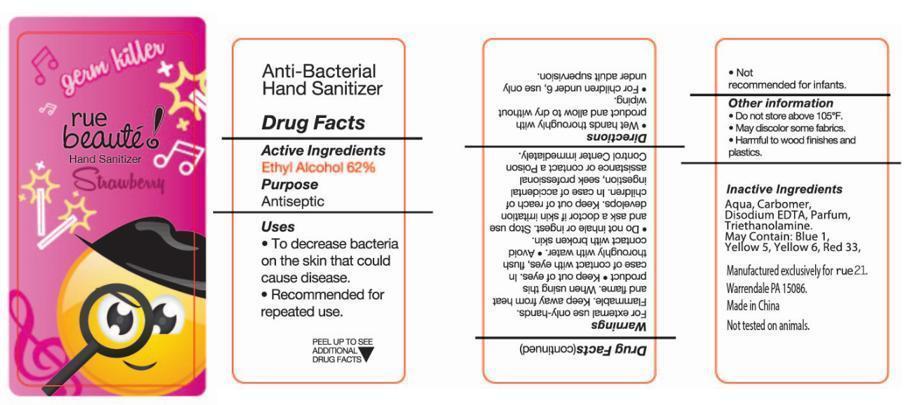 DRUG LABEL: RUE Beaute Strawberry Hand Sanitizer
NDC: 69933-102 | Form: LIQUID
Manufacturer: Pearl World INC.
Category: otc | Type: HUMAN OTC DRUG LABEL
Date: 20150810

ACTIVE INGREDIENTS: ALCOHOL 62 mL/100 mL
INACTIVE INGREDIENTS: WATER; CARBOMER COPOLYMER TYPE A; TROLAMINE; EDETATE DISODIUM; D&C RED NO. 33; FD&C BLUE NO. 1; FD&C YELLOW NO. 5; FD&C YELLOW NO. 6

Label

Active Ingredient

Ethyl Alcohol 62%

Purpose

Antiseptic

Uses

To decrease bacteria on the skin that could cause disease

Recommended for repeated use

WARNINGS

For external use only-hands

Flammable. Keep away from heat and flame when using this product

Keep out of eyes. In case of comtact with eyes, flush thoroughly with water

Avoid contact with broken skin

ASK DOCTOR

Do not inhale or ingest. Stop use and ask a doctor if skin irritation develops

Keep out of reach of children.

In case of accidental ingestion, seek professional assistance or contact a Poison Control Center immediately.

Directions

- Wet hands thoroughly with product and allow to dry without wiping
- For children under 6, use only under adult supervision
- Not recommended for infants

Other Information

Do not store above 105F

May discolor some fabrics

Harmful to wood finishes and plastics

Inactive Ingredient:

Aqua, Carbomer, Triethanolamine, Parfum, Disodium EDTA, may contain D and C Red No. 33, FD and C Blue No. 1, FD and C Yellow No. 5, FD and C Yellow No. 6.